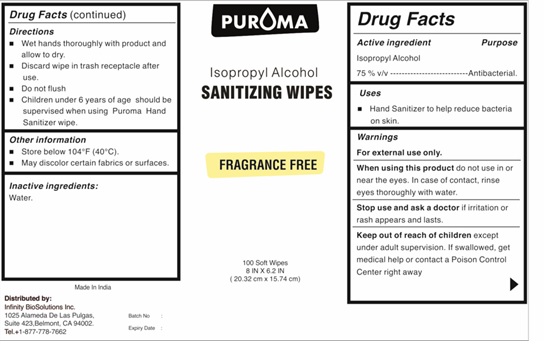 DRUG LABEL: PUROMA  IPA  Hand Sanitizer Wipe
NDC: 80948-019 | Form: CLOTH
Manufacturer: ZENITH MICRO CONTROL
Category: otc | Type: HUMAN OTC DRUG LABEL
Date: 20240201

ACTIVE INGREDIENTS: ISOPROPYL ALCOHOL 75 mL/100 mL
INACTIVE INGREDIENTS: WATER

Active ingredient

Isopropyl Alcohol 75% v/v.

Purpose

Antibacterial

Uses

Hand Sanitizer to help reduce bacteria on skin.

Warnings

• For external use only. Flammable. Keep away from fire or flame
• When using this productdo not use in or near the eyes. In case of contact, rinse eyes thoroughly with water.
• Stop use and ask a doctorif irritation or rash appears and lasts.

Keep out of reach of children

except under adult supervision. If swallowed, get medical help or contact a Poison Control Center right away.

Directions

• Wet hands thoroughly with product and allow to dry.
• Discard wipe in trash receptacle after use. Do not flush
• Children under 6 years of age should be supervised when using Puroma Hand Sanitizer wipe.

Other information

• Store below 104°F (40°C)

- May discolor certain fabrics or surfaces.

Inactive ingredients

Water